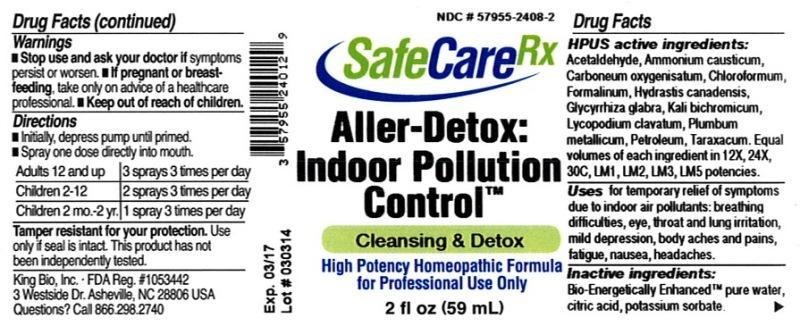 DRUG LABEL: Aller-Detox Indoor Pollution Control
NDC: 57955-2408 | Form: LIQUID
Manufacturer: King Bio Inc.
Category: homeopathic | Type: HUMAN OTC DRUG LABEL
Date: 20140321

ACTIVE INGREDIENTS: ACETALDEHYDE 12 [hp_X]/59 mL; AMMONIA 12 [hp_X]/59 mL; CARBON MONOXIDE 12 [hp_X]/59 mL; CHLOROFORM 12 [hp_X]/59 mL; FORMALDEHYDE 12 [hp_X]/59 mL; GOLDENSEAL 12 [hp_X]/59 mL; GLYCYRRHIZA GLABRA 12 [hp_X]/59 mL; POTASSIUM DICHROMATE 12 [hp_X]/59 mL; LYCOPODIUM CLAVATUM SPORE 12 [hp_X]/59 mL; LEAD 12 [hp_X]/59 mL; KEROSENE 12 [hp_X]/59 mL; TARAXACUM OFFICINALE 12 [hp_X]/59 mL
INACTIVE INGREDIENTS: WATER; CITRIC ACID MONOHYDRATE; POTASSIUM SORBATE

Aller-Detox: Indoor Pollution Control

Drug Facts

____________________________________________________________________________________________________________________

HPUS active ingredients: Acetaldehyde, Ammonium causticum, Carboneum oxygenisatum, Chloroformum, Formalinum, Hydrastis canadensis, Glycyrrhiza glabra, Kali bichromicum, Lycopodium clavatum, Plumbum metallicum, Petroleum, Taraxacum officinale. Equal volumes of each ingredient in 12X, 24X, 30C, LM1, LM2, LM3, LM5 potencies.

INDICATIONS AND USAGE

Uses for temporary relief of symptoms due to indoor air pollutants: breathing difficulies, eye, throat and lung irritation, mild depression, body aches and pains, fatigue, nausea, headaches.

INACTIVE INGREDIENT

Inactive ingredients: Bio-Energetically Enhanced pure water, citric acid, potassium sorbate.

Warnings

- Stop use and ask your doctor if symptoms persist or worsen.
- If pregnant or breast-feeding, take only on advice of a healthcare professional.

- Keep out of reach of children.

Directions:

- Initially, depress pump until primed.
- Spray one dose directly into mouth.
- Adults 12 and up 3 sprays 3 times per day.
- Children 2-12- 2 sprays 3 times per day.
- Children 2 mo.-2yr.- 1 spray 3 times per day.

OTHER SAFETY INFORMATION

Tamper resistant for your protection. Use only if safety seal is intact. This product has not been independently tested.

PURPOSE

Uses for temporary relief of symptoms due to indoor air pollutants:

- breathing difficulies
- eye, throat and lung irritation
- mild depression
- body aches and pains
- fatigue
- nausea
- headaches